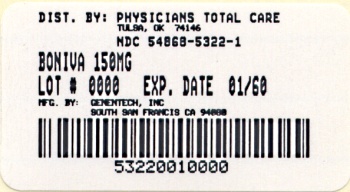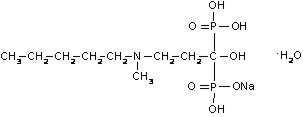 DRUG LABEL: Boniva
NDC: 54868-5322 | Form: TABLET, FILM COATED
Manufacturer: Physicians Total Care, Inc.
Category: prescription | Type: HUMAN PRESCRIPTION DRUG LABEL
Date: 20101202

ACTIVE INGREDIENTS: IBANDRONATE SODIUM 150 mg/1 1
INACTIVE INGREDIENTS: LACTOSE MONOHYDRATE; POVIDONE; CELLULOSE, MICROCRYSTALLINE; CROSPOVIDONE; STEARIC ACID; SILICON DIOXIDE; WATER; HYPROMELLOSES; TITANIUM DIOXIDE; TALC; POLYETHYLENE GLYCOL 6000

HIGHLIGHTS OF PRESCRIBING INFORMATION

These highlights do not include all the information needed to use BONIVA Tablets safely and effectively. See full prescribing information for BONIVA Tablets. BONIVA® (ibandronate sodium) Tablets Initial U.S. Approval: 2003

RECENT MAJOR CHANGES

Contraindications (4) | 1/2010
Warnings and Precautions (5.1) | 1/2010

1 INDICATIONS AND USAGE

BONIVA is a bisphosphonate indicated for the treatment and prevention of postmenopausal osteoporosis. (1.1)

2 DOSAGE AND ADMINISTRATION

One 150 mg tablet taken once monthly or one 2.5 mg tablet taken once daily (2.1)

Dosing instructions (2.2)

- Swallow whole tablet with 6-8 oz of plain water only, at least 60 minutes before the first food, beverage, or medication of the day.
- Do not lie down for at least 60 minutes after taking BONIVA.
- Do not eat, drink (except for water), or take other medication for 60 minutes after taking BONIVA.

3 DOSAGE FORMS AND STRENGTHS

Tablets: 2.5 mg, 150 mg (3)

4 CONTRAINDICATIONS

- Abnormalities of the esophagus which delay esophageal emptying such as stricture or achalasia (4, 5.1)
- Inability to stand or sit upright for at least 60 minutes (4, 5.1)
- Hypocalcemia (4)
- Hypersensitivity to BONIVA (4)

5 WARNINGS AND PRECAUTIONS

- Severe irritation of the upper gastrointestinal (GI) mucosa can occur. Dosing instructions should be followed and caution should be used in patients with active upper GI disease. Discontinue use if new or worsening symptoms occur. (5.1)
- Hypocalcemia may worsen during treatment. Correct hypocalcemia before use. (5.2)
- Severe bone, joint, and muscle pain may occur. Consider discontinuing use if symptoms develop. (5.3)
- Osteonecrosis of the jaw has been reported. (5.4)

6 ADVERSE REACTIONS

The most common adverse reactions (>5%) are back pain, dyspepsia, pain in extremity, diarrhea, headache, and myalgia. (6)

To report SUSPECTED ADVERSE REACTIONS, contact Genentech at 1-888-835-2555 or FDA at 1-800-FDA-1088 or www.fda.gov/medwatch.

7 DRUG INTERACTIONS

- Calcium supplements, antacids and some oral medications may interfere with absorption of ibandronate. (7.1)
- Use caution when co-prescribing aspirin/nonsteroidal anti-inflammatory drugs that may worsen gastrointestinal irritation. (7.2)

8 USE IN SPECIFIC POPULATIONS

BONIVA is not recommended in patients with severe renal impairment (creatinine clearance <30 mL/min). (5.5, 8.6)

FULL PRESCRIBING INFORMATION

RECENT MAJOR CHANGES

Enter section text here

1 INDICATIONS AND USAGE

Enter section text here

1.1 Treatment and Prevention of Postmenopausal Osteoporosis

BONIVA is indicated for the treatment and prevention of osteoporosis in postmenopausal women. BONIVA increases bone mineral density (BMD) and reduces the incidence of vertebral fractures.

2 DOSAGE AND ADMINISTRATION

Enter section text here

2.1 Dose

The dose of BONIVA is either one 150 mg tablet taken once monthly on the same date each month or one 2.5 mg tablet taken once daily.

2.2 Dosing Instructions

- To maximize absorption and clinical benefit, BONIVA should be taken at least 60 minutes before the first food or drink (other than water) of the day or before taking any oral medication or supplementation, including calcium, antacids, or vitamins (see DRUG INTERACTIONS [7.1]).
- To facilitate delivery to the stomach and thus reduce the potential for esophageal irritation, BONIVA tablets should be swallowed whole with a full glass of plain water (6 to 8 oz) while the patient is standing or sitting in an upright position. Patients should not lie down for 60 minutes after taking BONIVA (see WARNINGS AND PRECAUTIONS [5.1]).
- Patients should not eat, drink anything except water, or take other medications for at least 60 minutes after taking BONIVA.
- Plain water is the only drink that should be taken with BONIVA. Note that some mineral waters may have a higher concentration of calcium and therefore should not be used.
- Patients should not chew or suck the tablet because of a potential for oropharyngeal ulceration.
- The BONIVA 150 mg tablet should be taken on the same date each month (i.e., the patient's BONIVA day).
- The patient must not take two 150 mg tablets within the same week.
- If the once-monthly dose is missed, and the patient's next scheduled BONIVA day is more than 7 days away, the patient should be instructed to take one BONIVA 150 mg tablet in the morning following the date that it is remembered. The patient should then return to taking one BONIVA 150 mg tablet every month in the morning of their chosen day, according to their original schedule.
- If the once-monthly dose is missed, and the patient's next scheduled BONIVA day is only 1 to 7 days away, the patient must wait until the subsequent month's scheduled BONIVA day to take their tablet. The patient should then return to taking one BONIVA 150 mg tablet every month in the morning of their chosen day, according to their original schedule.

2.3 Recommendations for Calcium and Vitamin D Supplementation

Patients should receive supplemental calcium and vitamin D if dietary intake is inadequate (see DRUG INTERACTIONS [7.1]).

2.4 use in Specific Populations

BONIVA is not recommended for use in patients with severe renal impairment (creatinine clearance of <30 mL/min).

No dose adjustment is necessary for patients with mild or moderate renal impairment.

No dose adjustment is necessary for the elderly, or for patients with hepatic impairment.

3 DOSAGE FORMS AND STRENGTHS

Tablets, 2.5 mg and 150 mg

4 CONTRAINDICATIONS

- Abnormalities of the esophagus which delay esophageal emptying such as stricture or achalasia (see Upper Gastrointestinal Adverse Reactions [5.1])
- Inability to stand or sit upright for at least 60 minutes (see Dosing Instructions [2.2], Upper Gastrointestinal Adverse Reactions [5.1])
- Hypocalcemia (see WARNINGS AND PRECAUTIONS [5.2])
- Known hypersensitivity to BONIVA or to any of its excipients (see ADVERSE REACTIONS [6.2]).

5 WARNINGS AND PRECAUTIONS

Enter section text here

5.1 Upper Gastrointestinal Adverse Reactions

BONIVA, like other bisphosphonates administered orally, may cause local irritation of the upper gastrointestinal mucosa. Because of these possible irritant effects and a potential for worsening of the underlying disease, caution should be used when BONIVA is given to patients with active upper gastrointestinal problems (such as known Barrett's esophagus, dysphagia, other esophageal diseases, gastritis, duodenitis or ulcers).

Esophageal adverse experiences, such as esophagitis, esophageal ulcers and esophageal erosions, occasionally with bleeding and rarely followed by esophageal stricture or perforation, have been reported in patients receiving treatment with oral bisphosphonates. In some cases, these have been severe and required hospitalization. Physicians should therefore be alert to any signs or symptoms signaling a possible esophageal reaction and patients should be instructed to discontinue BONIVA and seek medical attention if they develop dysphagia, odynophagia, retrosternal pain or new or worsening heartburn.

The risk of severe esophageal adverse experiences appears to be greater in patients who lie down after taking oral bisphosphonates and/or who fail to swallow it with the recommended full glass (6-8 oz) of water, and/or who continue to take oral bisphosphonates after developing symptoms suggestive of esophageal irritation. Therefore, it is very important that the full dosing instructions are provided to, and understood by, the patient (see DOSAGE AND ADMINISTRATION [2.2]). In patients who cannot comply with dosing instructions due to mental disability, therapy with BONIVA should be used under appropriate supervision.

There have been post-marketing reports of gastric and duodenal ulcers with oral bisphosphonate use, some severe and with complications, although no increased risk was observed in controlled clinical trials.

5.2 Hypocalcemia and Mineral Metabolsim

Treat hypocalcemia and other disturbances of bone and mineral metabolism before starting BONIVA therapy. Adequate intake of calcium and vitamin D is important in all patients to prevent hypocalcemia (see DOSAGE AND ADMINISTRATION [2.3]). Hypocalcemia following dosing has been reported postmarketing.

5.3 Musculoskeletal Pain

Severe and occasionally incapacitating bone, joint, and/or muscle pain has been reported in patients taking BONIVA and other bisphosphonates (see ADVERSE REACTIONS [6]). The time to onset of symptoms varied from one day to several months after starting the drug. Most patients had relief of symptoms after stopping. A subset had recurrence of symptoms when rechallenged with the same drug or another bisphosphonate. Consider discontinuing use if severe symptoms develop.

5.4 Jaw Osteonecrosis

Osteonecrosis, primarily in the jaw, has been reported in patients treated with bisphosphonates. Most cases have been in cancer patients undergoing dental procedures, but some have occurred in patients with postmenopausal osteoporosis or other diagnoses. Known risk factors for osteonecrosis include a diagnosis of cancer, concomitant therapies (e.g., chemotherapy, radiotherapy, corticosteroids), and co-morbid disorders (e.g., anemia, coagulopathy, infection, pre-existing dental disease). Most reported cases have been in patients treated with bisphosphonates intravenously but some have been in patients treated orally (see ADVERSE REACTIONS [6.2]).

For patients who develop osteonecrosis of the jaw (ONJ) while on bisphosphonate therapy, dental surgery may exacerbate the condition. For patients requiring dental procedures, there are no data available to suggest whether discontinuation of bisphosphonate treatment reduces the risk of ONJ. Clinical judgment of the treating physician should guide the management plan of each patient based on individual benefit/risk assessment.

5.5 Severe Renal Impairment

BONIVA is not recommended for use in patients with severe renal impairment (creatinine clearance of <30 mL/min).

6 ADVERSE REACTIONS

Enter section text here

6.1 Clinical Trials Experience

Because clinical trials are conducted under widely varying conditions, adverse reaction rates observed in the clinical trials of a drug cannot be directly compared to rates in the clinical trials of another drug and may not reflect the rates observed in practice.

Treatment and Prevention of Postmenopausal Osteoporosis

Daily Dosing

The safety of BONIVA 2.5 mg once daily in the treatment and prevention of postmenopausal osteoporosis was assessed in 3577 patients aged 41 – 82 years. The duration of the trials was 2 to 3 years, with 1134 patients exposed to placebo and 1140 exposed to BONIVA 2.5 mg. Patients with pre-existing gastrointestinal disease and concomitant use of non-steroidal anti-inflammatory drugs, proton pump inhibitors and H2 antagonists were included in these clinical trials. All patients received 500 mg calcium plus 400 IU vitamin D supplementation daily.

The incidence of all-cause mortality was 1% in the placebo group and 1.2% in the BONIVA 2.5 mg daily group. The incidence of serious adverse events was 20% in the placebo group and 23% in the BONIVA 2.5 mg daily group. The percentage of patients who withdrew from treatment due to adverse events was approximately 17% in both the BONIVA 2.5 mg daily group and the placebo group. Table 1 lists adverse events from the treatment and prevention studies reported in ≥2% of patients and more frequently in patients treated daily with BONIVA than patients treated with placebo.

Table 1 Adverse Events Occurring at a Frequency ≥2% and More Frequently in Patients Treated with BONIVA than in Patients Treated with Placebo Daily in the Osteoporosis Treatment and Prevention Studies
Body System | Placebo % (n=1134) | BONIVA 2.5 mg % (n=1140)
Body as a Whole
Back Pain | 12.2 | 13.5
Pain in Extremity | 6.4 | 7.8
Infection | 3.4 | 4.3
Asthenia | 2.3 | 3.5
Allergic Reaction | 1.9 | 2.5
Digestive System
Dyspepsia | 9.8 | 11.9
Diarrhea | 5.0 | 6.8
Tooth Disorder | 2.3 | 3.5
Vomiting | 2.1 | 2.7
Gastritis | 1.9 | 2.2
Metabolic and Nutritional Disorders
Hypercholesterolemia | 4.2 | 4.8
Musculoskeletal System
Myalgia | 5.1 | 5.7
Joint Disorder | 3.3 | 3.6
Arthritis | 2.7 | 3.2
Nervous System
Headache | 5.8 | 6.5
Dizziness | 2.6 | 3.7
Vertigo | 2.5 | 3.0
Nerve Root Lesion | 1.9 | 2.2
Respiratory System
Upper Respiratory Infection | 33.2 | 33.7
Bronchitis | 6.8 | 10.0
Pneumonia | 4.3 | 5.9
Pharyngitis | 1.5 | 2.5
Urogenital System
Urinary Tract Infection | 4.2 | 5.5

Gastrointestinal Adverse Events

The incidence of adverse events in the placebo and BONIVA 2.5 mg daily groups were: dyspepsia (10% vs. 12%), diarrhea (5% vs. 7%), and abdominal pain (5% vs. 6%).

Musculoskeletal Adverse Events

The incidence of adverse events in the placebo and BONIVA 2.5 mg daily groups were: back pain (12% vs. 14%), arthralgia (14% vs. 14%) and myalgia (5% vs. 6%).

Ocular Adverse Events

Reports in the medical literature indicate that bisphosphonates may be associated with ocular inflammation such as iritis and scleritis. In some cases, these events did not resolve until the bisphosphonate was discontinued. There were no reports of ocular inflammation in studies with BONIVA 2.5 mg daily.

Monthly Dosing

The safety of BONIVA 150 mg once monthly in the treatment of postmenopausal osteoporosis was assessed in a two year trial which enrolled 1583 patients aged 54 – 81 years, with 395 patients exposed to BONIVA 2.5 mg daily and 396 exposed to BONIVA 150 mg monthly. Patients with active or significant pre-existing gastrointestinal disease were excluded from this trial. Patients with dyspepsia or concomitant use of non-steroidal anti-inflammatory drugs, proton pump inhibitors and H2 antagonists were included in this study. All patients received 500 mg calcium plus 400 IU vitamin D supplementation daily.

After one year, the incidence of all-cause mortality was 0.3% in both the BONIVA 2.5 mg daily group and the BONIVA 150 mg monthly group. The incidence of serious adverse events was 5% in the BONIVA 2.5 mg daily group and 7% in the BONIVA 150 mg monthly group. The percentage of patients who withdrew from treatment due to adverse events was 9% in the BONIVA 2.5 mg daily group and 8% in the BONIVA 150 mg monthly group. Table 2 lists the adverse events reported in ≥2% of patients.

Table 2 Adverse Events with an Incidence of at Least 2% in Patients Treated with BONIVA 2.5 mg Daily or 150 mg Once-Monthly for Treatment of Postmenopausal Osteoporosis
Body System/Adverse Event | BONIVA 2.5 mg Daily % (n=395) | BONIVA 150 mg Monthly % (n=396)
Vascular Disorders
Hypertension | 7.3 | 6.3
Gastrointestinal Disorders
Dyspepsia | 7.1 | 5.6
Nausea | 4.8 | 5.1
Diarrhea | 4.1 | 5.1
Constipation | 2.5 | 4.0
Abdominal Pain* | 5.3 | 7.8
Musculoskeletal and Connective Tissue Disorders
Arthralgia | 3.5 | 5.6
Back Pain | 4.3 | 4.5
Pain in Extremity | 1.3 | 4.0
Localized Osteoarthritis | 1.3 | 3.0
Myalgia | 0.8 | 2.0
Muscle Cramp | 2.0 | 1.8
Infections and Infestations
Influenza | 3.8 | 4.0
Nasopharyngitis | 4.3 | 3.5
Bronchitis | 3.5 | 2.5
Urinary Tract Infection | 1.8 | 2.3
Upper Respiratory Tract Infection | 2.0 | 2.0
Nervous System Disorders
Headache | 4.1 | 3.3
Dizziness | 1.0 | 2.3
General Disorders and Administration Site Conditions
Influenza-like Illness† | 0.8 | 3.3
Skin and Subcutaneous Tissue Disorders
Rash‡ | 1.3 | 2.3
Psychiatric Disorders
Insomnia | 0.8 | 2.0

*Combination of abdominal pain and abdominal pain upper†Combination of influenza-like illness and acute phase reaction‡Combination of rash pruritic, rash macular, rash papular, rash generalized, rash erythematous, dermatitis, dermatitis allergic, dermatitis medicamentosa, erythema and exanthem

Gastrointestinal Adverse Events

The incidence of adverse events in the BONIVA 2.5 mg daily and BONIVA 150 mg monthly groups were: dyspepsia (7% vs. 6%), diarrhea (4% vs. 5%), and abdominal pain (5% vs. 8%).

Musculoskeletal Adverse Events

The incidence of adverse events in the BONIVA 2.5 mg daily and BONIVA 150 mg monthly groups were: back pain (4% vs. 5%), arthralgia (4% vs. 6%) and myalgia (1% vs. 2%).

Acute Phase Reactions

Symptoms consistent with acute phase reactions have been reported with bisphosphonate use. Over the two years of the study, the overall incidence of acute phase reaction symptoms was 3% in the BONIVA 2.5 mg daily group and 9% in the BONIVA 150 mg monthly group. These incidence rates are based on the reporting of any of 33 acute-phase reaction like symptoms within 3 days of the monthly dosing and lasting 7 days or less. Influenza like illness was reported in no patients in the BONIVA 2.5 mg daily group and 2% in the BONIVA 150 mg monthly group.

Ocular Adverse Events

Two patients who received BONIVA 150 mg once-monthly experienced ocular inflammation, one was a case of uveitis and the other scleritis.

One hundred sixty (160) postmenopausal women without osteoporosis participated in a 1-year, double-blind, placebo-controlled study of BONIVA 150 mg once-monthly for prevention of bone loss. Seventy-seven subjects received BONIVA and 83 subjects received placebo. The overall pattern of adverse events was similar to that previously observed.

6.2 Postmarketing Experience

The following adverse reactions have been identified during postapproval use of BONIVA. Because these reactions are reported voluntarily from a population of uncertain size, it is not always possible to reliably estimate their frequency or establish a causal relationship to drug exposure.

Hypersensitivity

Allergic reactions including anaphylaxis, angioedema, bronchospasm and rash have been reported (see CONTRAINDICATIONS [4]).

Hypocalcemia

Hypocalcemia has been reported in patients treated with BONIVA (see WARNINGS AND PRECAUTIONS [5.2]).

Musculoskeletal Pain

Bone, joint, or muscle pain (musculoskeletal pain), described as severe or incapacitating, has been reported (see WARNINGS AND PRECAUTIONS [5.3]).

Jaw Osteonecrosis

Osteonecrosis of the jaw has been reported in patients treated with BONIVA (see WARNINGS AND PRECAUTIONS [5.4]).

7 DRUG INTERACTIONS

Enter section text here

7.1 Calcium Supplements/Antacids

Products containing calcium and other multivalent cations (such as aluminum, magnesium, iron) are likely to interfere with absorption of BONIVA. BONIVA should be taken at least 60 minutes before any oral medications, including medications containing multivalent cations (such as antacids, supplements or vitamins). Also, patients should wait at least 60 minutes after dosing before taking any other oral medications (see PATIENT COUNSELING INFORMATION [17.1]).

7.2 Aspirin/Nonsteroidal Anti-Inflammatory Drugs (NSAIDs)

Because aspirin, NSAIDs, and bisphosphonates are all associated with gastrointestinal irritation, caution should be exercised in the concomitant use of aspirin or NSAIDs with BONIVA.

7.3 H2 Blockers

In healthy volunteers, co-administration with ranitidine resulted in a 20% increased bioavailability of ibandronate, which was not considered to be clinically relevant (see CLINICAL PHARMACOLOGY [12.3]).

7.4 Drug/Laboratory Test Interactions

Bisphosphonates are known to interfere with the use of bone-imaging agents. Specific studies with ibandronate have not been performed.

8 USE IN SPECIFIC POPULATIONS

Enter section text here

8.1 Pregnancy: Category C

There are no adequate and well-controlled studies in pregnant women. BONIVA should be used during pregnancy only if the potential benefit justifies the potential risk to the mother and fetus.

Bisphosphonates are incorporated into the bone matrix, from where they are gradually released over periods of weeks to years. The extent of bisphosphonate incorporation into adult bone, and hence, the amount available for release back into the systemic circulation, is directly related to the total dose and duration of bisphosphonate use. Although there are no data on fetal risk in humans, bisphosphonates do cause fetal harm in animals, and animal data suggest that uptake of bisphosphonates into fetal bone is greater than into maternal bone. Therefore, there is a theoretical risk of fetal harm (e.g., skeletal and other abnormalities) if a woman becomes pregnant after completing a course of bisphosphonate therapy. The impact of variables such as time between cessation of bisphosphonate therapy to conception, the particular bisphosphonate used, and the route of administration (intravenous versus oral) on this risk has not been established.

In female rats given ibandronate orally at doses ≥3 times human exposure at the recommended daily oral dose of 2.5 mg or ≥1 times human exposure at the recommended once-monthly oral dose of 150 mg beginning 14 days before mating and continuing through lactation, maternal deaths were observed at the time of delivery in all dose groups. Perinatal pup loss in dams given 45 times human exposure at the recommended daily dose and 13 times the recommended once-monthly dose was likely related to maternal dystocia. Calcium supplementation did not completely prevent dystocia and periparturient mortality in any of the treated groups at ≥16 times the recommended daily dose and ≥4.6 times the recommended once-monthly dose. A low incidence of postimplantation loss was observed in rats treated from 14 days before mating throughout lactation or during gestation, only at doses causing maternal dystocia and periparturient mortality. In pregnant rats dosed orally from gestation day 17 through lactation day 21 (following closure of the hard palate through weaning), maternal toxicity, including dystocia and mortality, fetal perinatal and postnatal mortality, were observed at doses equivalent to human exposure at the recommended daily and ≥4 times the recommended once-monthly dose. Periparturient mortality has also been observed with other bisphosphonates and appears to be a class effect related to inhibition of skeletal calcium mobilization resulting in hypocalcemia and dystocia (see NONCLINICAL TOXICOLOGY [13.2]).

Exposure of pregnant rats during the period of organogenesis resulted in an increased fetal incidence of RPU (renal pelvis ureter) syndrome at oral doses 30 times the human exposure at the recommended daily oral dose of 2.5 mg and ≥9 times the recommended once-monthly oral dose of 150 mg. Impaired pup neuromuscular development (cliff avoidance test) was observed at 45 times human exposure at the daily dose and 13 times the once-monthly dose (see NONCLINICAL TOXICOLOGY [13.2]).

In pregnant rabbits treated orally with ibandronate during gestation at doses ≥8 times the recommended human daily oral dose of 2.5 mg and ≥4 times the recommended human once-monthly oral dose of 150 mg, dose-related maternal mortality was observed in all treatment groups. The deaths occurred prior to parturition and were associated with lung edema and hemorrhage. No significant fetal anomalies were observed (see NONCLINICAL TOXICOLOGY [13.2]).

8.3 Nursing Mothers

It is not known whether BONIVA is excreted in human milk. Because many drugs are excreted in human milk, caution should be exercised when BONIVA is administered to a nursing woman. In lactating rats treated with intravenous doses, ibandronate was present in breast milk from 2 to 24 hours after dose administration. Concentrations in milk averaged 1.5 times plasma concentrations.

8.4 Pediatric Use

Safety and effectiveness in pediatric patients have not been established.

8.5 Geriatric Use

Of the patients receiving BONIVA 2.5 mg daily in postmenopausal osteoporosis studies, 52% were over 65 years of age, and 10% were over 75 years of age. Of the patients receiving BONIVA 150 mg once-monthly in the postmenopausal osteoporosis 1-year study, 52% were over 65 years of age, and 9% were over 75 years of age. No overall differences in effectiveness or safety were observed between these patients and younger patients but greater sensitivity in some older individuals cannot be ruled out.

8.6 Renal Impairment

BONIVA is not recommended for use in patients with severe renal impairment (creatinine clearance <30 mL/min).

10 OVERDOSAGE

No specific information is available on the treatment of overdosage of BONIVA. However, based on knowledge of this class of compounds, oral overdosage may result in hypocalcemia, hypophosphatemia, and upper gastrointestinal adverse events, such as upset stomach, dyspepsia, esophagitis, gastritis, or ulcer. Milk or antacids should be given to bind BONIVA. Due to the risk of esophageal irritation, vomiting should not be induced, and the patient should remain fully upright. Dialysis would not be beneficial.

11 DESCRIPTION

BONIVA (ibandronate sodium) is a nitrogen-containing bisphosphonate that inhibits osteoclast-mediated bone resorption. The chemical name for ibandronate sodium is 3-(N-methyl-N-pentyl) amino-1-hydroxypropane-1,1-diphosphonic acid, monosodium salt, monohydrate with the molecular formula C9H22NO7P2Na•H2O and a molecular weight of 359.24. Ibandronate sodium is a white- to off-white powder. It is freely soluble in water and practically insoluble in organic solvents. Ibandronate sodium has the following structural formula:

BONIVA is available as a white, oblong, 2.5 mg film-coated tablet for daily oral administration or as a white, oblong, 150 mg film-coated tablet for once-monthly oral administration. One 2.5 mg film-coated tablet contains 2.813 mg ibandronate monosodium monohydrate, equivalent to 2.5 mg free acid. One 150 mg film-coated tablet contains 168.75 mg ibandronate monosodium monohydrate, equivalent to 150 mg free acid. BONIVA also contains the following inactive ingredients: lactose monohydrate, povidone, microcrystalline cellulose, crospovidone, purified stearic acid, colloidal silicon dioxide, and purified water. The tablet film coating contains hypromellose, titanium dioxide, talc, polyethylene glycol 6000, and purified water.

12 CLINICAL PHARMACOLOGY

Enter section text here

12.1 Mechanism of Action

The action of ibandronate on bone tissue is based on its affinity for hydroxyapatite, which is part of the mineral matrix of bone. Ibandronate inhibits osteoclast activity and reduces bone resorption and turnover. In postmenopausal women, it reduces the elevated rate of bone turnover, leading to, on average, a net gain in bone mass.

12.2 Pharmacodynamics

Osteoporosis is characterized by decreased bone mass and increased fracture risk, most commonly at the spine, hip, and wrist. The diagnosis can be confirmed by a finding of low bone mass, evidence of fracture on x-ray, a history of osteoporotic fracture, or height loss or kyphosis indicative of vertebral fracture. While osteoporosis occurs in both men and women, it is most common among women following menopause. In healthy humans, bone formation and resorption are closely linked; old bone is resorbed and replaced by newly formed bone. In postmenopausal osteoporosis, bone resorption exceeds bone formation, leading to bone loss and increased risk of fracture. After menopause, the risk of fractures of the spine and hip increases; approximately 40% of 50-year-old women will experience an osteoporosis-related fracture during their remaining lifetimes.

BONIVA produced biochemical changes indicative of dose-dependent inhibition of bone resorption, including decreases of biochemical markers of bone collagen degradation (such as deoxypyridinoline, and cross-linked C-telopeptide of Type I collagen) in the daily dose range of 0.25 mg to 5 mg and once-monthly doses from 100 mg to 150 mg in postmenopausal women.

Treatment with 2.5 mg daily BONIVA resulted in decreases in biochemical markers of bone turnover, including urinary C-terminal telopeptide of Type I collagen (uCTX) and serum osteocalcin, to levels similar to those in premenopausal women. Changes in markers of bone formation were observed later than changes in resorption markers, as expected, due to the coupled nature of bone resorption and formation. Treatment with 2.5 mg daily BONIVA decreased levels of uCTX within 1 month of starting treatment and decreased levels of osteocalcin within 3 months. Bone turnover markers reached a nadir of approximately 64% below baseline values by 6 months of treatment and remained stable with continued treatment for up to 3 years. Following treatment discontinuation, there is a return to pretreatment baseline rates of elevated bone resorption associated with postmenopausal osteoporosis.

In a 1-year, study comparing once-monthly vs. once-daily oral dosing regimens, the median decrease from baseline in serum CTX values was -76% for patients treated with the 150 mg once-monthly regimen and -67% for patients treated with the 2.5 mg daily regimen. In a 1-year, prevention study comparing BONIVA 150 mg once-monthly to placebo, the median placebo-subtracted decrease in sCTX was -49.8%.

12.3 Pharmacokinetics

Absorption

The absorption of oral ibandronate occurs in the upper gastrointestinal tract. Plasma concentrations increase in a dose-linear manner up to 50 mg oral intake and increases nonlinearly above this dose.

Following oral dosing, the time to maximum observed plasma ibandronate concentrations ranged from 0.5 to 2 hours (median 1 hour) in fasted healthy postmenopausal women. The mean oral bioavailability of 2.5 mg ibandronate was about 0.6% compared to intravenous dosing. The extent of absorption is impaired by food or beverages (other than plain water). The oral bioavailability of ibandronate is reduced by about 90% when BONIVA is administered concomitantly with a standard breakfast in comparison with bioavailability observed in fasted subjects. There is no meaningful reduction in bioavailability when ibandronate is taken at least 60 minutes before a meal. However, both bioavailability and the effect on bone mineral density (BMD) are reduced when food or beverages are taken less than 60 minutes following an ibandronate dose.

Distribution

After absorption, ibandronate either rapidly binds to bone or is excreted into urine. In humans, the apparent terminal volume of distribution is at least 90 L, and the amount of dose removed from the circulation via the bone is estimated to be 40% to 50% of the circulating dose. In vitro protein binding in human serum was 99.5% to 90.9% over an ibandronate concentration range of 2 to 10 ng/mL in one study and approximately 85.7% over a concentration range of 0.5 to 10 ng/mL in another study.

Metabolism

Ibandronate does not undergo hepatic metabolism and does not inhibit the hepatic cytochrome P450 system. Ibandronate is eliminated by renal excretion. Based on a rat study, the ibandronate secretory pathway does not appear to include known acidic or basic transport systems involved in the excretion of other drugs. There is no evidence that ibandronate is metabolized in humans.

Elimination

The portion of ibandronate that is not removed from the circulation via bone absorption is eliminated unchanged by the kidney (approximately 50% to 60% of the absorbed dose). Unabsorbed ibandronate is eliminated unchanged in the feces.

The plasma elimination of ibandronate is multiphasic. Its renal clearance and distribution into bone accounts for a rapid and early decline in plasma concentrations, reaching 10% of the Cmax within 3 or 8 hours after intravenous or oral administration, respectively. This is followed by a slower clearance phase as ibandronate redistributes back into the blood from bone. The observed apparent terminal half-life for ibandronate is generally dependent on the dose studied and on assay sensitivity. The observed apparent terminal half-life for the 150 mg ibandronate tablet upon oral administration to healthy postmenopausal women ranges from 37 to 157 hours.

Total clearance of ibandronate is low, with average values in the range 84 to 160 mL/min. Renal clearance (about 60 mL/min in healthy postmenopausal females) accounts for 50% to 60% of total clearance and is related to creatinine clearance. The difference between the apparent total and renal clearances likely reflects bone uptake of the drug.

Specific Populations

Pediatrics

The pharmacokinetics of ibandronate has not been studied in patients <18 years of age.

Geriatric

Because ibandronate is not known to be metabolized, the only difference in ibandronate elimination for geriatric patients versus younger patients is expected to relate to progressive age-related changes in renal function.

Gender

The bioavailability and pharmacokinetics of ibandronate are similar in both men and women.

Race

Pharmacokinetic differences due to race have not been studied.

Renal Impairment

Renal clearance of ibandronate in patients with various degrees of renal impairment is linearly related to creatinine clearance (CLcr).

Following a single dose of 0.5 mg ibandronate by intravenous administration, patients with CLcr 40 to 70 mL/min had 55% higher exposure (AUC∞) than the exposure observed in subjects with CLcr >90 mL/min. Patients with CLcr <30 mL/min had more than a two-fold increase in exposure compared to the exposure for healthy subjects (see DOSAGE AND ADMINISTRATION [2.4]).

Hepatic Impairment

No studies have been performed to assess the pharmacokinetics of ibandronate in patients with hepatic impairment because ibandronate is not metabolized in the human liver.

Drug Interactions

Products containing calcium and other multivalent cations (such as aluminum, magnesium, iron), including milk, food, and antacids are likely to interfere with absorption of ibandronate, which is consistent with findings in animal studies.

H2 Blockers

A pharmacokinetic interaction study in healthy volunteers demonstrated that 75 mg ranitidine (25 mg injected intravenously 90 and 15 minutes before and 30 minutes after ibandronate administration) increased the oral bioavailability of 10 mg ibandronate by about 20%. This degree of increase is not considered to be clinically relevant.

13 NONCLINICAL TOXICOLOGY

Enter section text here

13.1 Carcinogenesis, Mutagenesis, Impairment of Fertility

Carcinogenesis

In a 104-week carcinogenicity study, doses of 3, 7, or 15 mg/kg/day were administered by oral gavage to male and female Wistar rats (systemic exposures up to 12 and 7 times, respectively, human exposure at the recommended daily oral dose of 2.5 mg, and cumulative exposures up to 3.5 and 2 times, respectively, human exposure at the recommended once-monthly oral dose of 150 mg, based on AUC comparison). There were no significant drug-related tumor findings in male or female rats. In a 78-week carcinogenicity study, doses of 5, 20, or 40 mg/kg/day were administered by oral gavage to male and female NMRI mice (exposures up to 475 and 70 times, respectively, human exposure at the recommended daily oral dose of 2.5 mg and cumulative exposures up to 135 and 20 times, respectively, human exposure at the recommended once-monthly oral dose of 150 mg, based on AUC comparison). There were no significant drug-related tumor findings in male or female mice. In a 90-week carcinogenicity study, doses of 5, 20, or 80 mg/kg/day were administered in the drinking water to NMRI mice (cumulative monthly exposures in males and females up to 70 and 115 times, respectively, human exposure at the recommended dose of 150 mg, based on AUC comparison). A dose-related increased incidence of adrenal subcapsular adenoma/carcinoma was observed in female mice, which was statistically significant at 80 mg/kg/day (220 to 400 times human exposure at the recommended daily oral dose of 2.5 mg and 115 times human exposure at the recommended once-monthly oral dose of 150 mg, based on AUC comparison). The relevance of these findings to humans is unknown.

Mutagenesis

There was no evidence for a mutagenic or clastogenic potential of ibandronate in the following assays: in vitro bacterial mutagenesis assay in Salmonella typhimurium and Escherichia coli (Ames test), mammalian cell mutagenesis assay in Chinese hamster V79 cells, and chromosomal aberration test in human peripheral lymphocytes, each with and without metabolic activation. Ibandronate was not genotoxic in the in vivo mouse micronucleus tests for chromosomal damage.

Impairment of Fertility

In female rats treated from 14 days prior to mating through gestation, decreases in fertility, corpora lutea, and implantation sites were observed at an oral dose of 16 mg/kg/day (45 times human exposure at the recommended daily oral dose of 2.5 mg and 13 times human exposure at the recommended once-monthly oral dose of 150 mg, based on AUC comparison).

13.2 Animal Reproductive and Developmental Toxicology

In female rats given oral doses of 1, 4, or 16 mg/kg/day beginning 14 days before mating and continuing through lactation, maternal deaths were observed at the time of delivery in all dose groups (≥3 times human exposure at the recommended daily oral dose of 2.5 mg or ≥1 times human exposure at the recommended once-monthly oral dose of 150 mg, based on AUC comparison). Perinatal pup loss in dams given 16 mg/kg/day (45 times human exposure at the recommended daily oral dose of 2.5 mg and 13 times human exposure at the recommended once-monthly oral dose of 150 mg, based on AUC comparison) was likely related to maternal dystocia. In pregnant rats given oral doses of 6, 20, or 60 mg/kg/day during gestation, calcium supplementation (32 mg/kg/day by subcutaneous injection from gestation day 18 to parturition) did not completely prevent dystocia and periparturient mortality in any of the treated groups (≥16 times human exposure at the recommended daily oral dose of 2.5 mg and ≥4.6 times human exposure at the recommended once-monthly oral dose of 150 mg, based on AUC comparison). A low incidence of postimplantation loss was observed in rats treated from 14 days before mating throughout lactation or during gestation, only at doses causing maternal dystocia and periparturient mortality. In pregnant rats dosed orally with 1, 5, or 20 mg/kg/day from gestation day 17 through lactation day 21 (following closure of the hard palate through weaning), maternal toxicity, including dystocia and mortality, fetal perinatal and postnatal mortality, were observed at doses ≥5 mg/kg/day (equivalent to human exposure at the recommended daily oral dose of 2.5 mg and ≥4 times human exposure at the recommended once-monthly oral dose of 150 mg, based on AUC comparison). Periparturient mortality has also been observed with other bisphosphonates and appears to be a class effect related to inhibition of skeletal calcium mobilization resulting in hypocalcemia and dystocia.

Exposure of pregnant rats during the period of organogenesis resulted in an increased fetal incidence of RPU (renal pelvis ureter) syndrome at oral doses ≥10 mg/kg/day (≥30 times human exposure at the recommended daily oral dose of 2.5 mg and ≥9 times human exposure at the recommended once-monthly oral dose of 150 mg, based on AUC comparison). Impaired pup neuromuscular development (cliff avoidance test) was observed at 16 mg/kg/day when dams were dosed from 14 days before mating through lactation (45 times human exposure at the recommended daily oral dose of 2.5 mg and 13 times human exposure at the recommended once-monthly oral dose of 150 mg, based on AUC comparison).

In pregnant rabbits given oral doses of 1, 4, or 20 mg/kg/day during gestation, dose-related maternal mortality was observed in all treatment groups (≥8 times the recommended human daily oral dose of 2.5 mg and ≥4 times the recommended human once-monthly oral dose of 150 mg, based on body surface area comparison, mg/m^2). The deaths occurred prior to parturition and were associated with lung edema and hemorrhage. No significant fetal anomalies were observed.

13.3 Animal Pharmacology

Animal studies have shown that ibandronate is an inhibitor of osteoclast-mediated bone resorption. In the Schenk assay in growing rats, ibandronate inhibited bone resorption and increased bone volume, based on histologic examination of the tibial metaphyses. There was no evidence of impaired mineralization at the highest dose of 5 mg/kg/day (subcutaneously), which is 1000 times the lowest antiresorptive dose of 0.005 mg/kg/day in this model, and 5000 times the optimal antiresorptive dose of 0.001 mg/kg/day in the aged ovariectomized rat. This indicates that BONIVA administered at therapeutic doses is unlikely to induce osteomalacia.

Long-term daily or once-monthly intermittent administration of ibandronate to ovariectomized rats or monkeys was associated with suppression of bone turnover and increases in bone mass. In both rats and monkeys, vertebral BMD, trabecular density, and biomechanical strength were increased dose-dependently at doses up to 15 times the recommended human daily oral dose of 2.5 mg, or cumulative monthly doses up to 8 times (rat) or 6 times (monkey) the recommended human once-monthly oral dose of 150 mg, based on body surface area (mg/m^2) or AUC comparison. In monkeys, ibandronate maintained the positive correlation between bone mass and strength at the ulna and femoral neck. New bone formed in the presence of ibandronate had normal histologic structure and did not show mineralization defects.

14 CLINICAL STUDIES

Enter section text here

14.1 Treatment of Postmenopausal Osteoporosis

Daily Dosing

The effectiveness and safety of BONIVA were demonstrated in a randomized, double-blind, placebo-controlled, multinational study (Treatment Study) of 2946 women aged 55 to 80 years, who were on average 21 years postmenopause, who had lumbar spine BMD 2 to 5 SD below the premenopausal mean (T-score) in at least one vertebra [L1-L4], and who had 1 to 4 prevalent vertebral fractures. BONIVA was evaluated at oral doses of 2.5 mg daily and 20 mg intermittently. The main outcome measure was the occurrence of new radiographically diagnosed vertebral fractures after 3 years of treatment. The diagnosis of an incident vertebral fracture was based on both qualitative diagnosis by the radiologist and quantitative morphometric criterion. The morphometric criterion required the dual occurrence of 2 events: a relative height ratio or relative height reduction in a vertebral body of at least 20%, together with at least a 4 mm absolute decrease in height. All women received 400 IU vitamin D and 500 mg calcium supplementation per day.

Effect on Fracture Incidence

BONIVA 2.5 mg daily significantly reduced the incidence of new vertebral (primary efficacy measure) and of new and worsening vertebral fractures. Over the course of the 3-year study, the risk for vertebral fracture was 9.6% in the placebo-treated women and 4.7% in the women treated with BONIVA 2.5 mg (p<0.001) (see Table 3).

Table 3 Effect of BONIVA on the Incidence of Vertebral Fracture in the 3-Year Osteoporosis Treatment Study*
 | Proportion of Patients with Fracture (%)
 | Placebo n=975 | BONIVA 2.5 mg Daily n=977 | Absolute Risk Reduction (%) 95% CI | Relative Risk Reduction (%) 95% CI
New Vertebral Fracture | 9.6 | 4.7 | 4.9 | 52 †
0-3 Year |  |  | (2.3, 7.4) | (29, 68)
New and Worsening Vertebral Fracture | 10.4 | 5.1 | 5.3 | 52
0-3 Year |  |  | (2.6, 7.9) | (30, 67)
Clinical (Symptomatic) Vertebral Fracture | 5.3 | 2.8 | 2.5 | 49
0-3 Year |  |  | (0.6, 4.5) | (14, 69)

*The endpoint value is the value at the study's last time point, 3 years, for all patients who had a fracture identified at that time; otherwise, the last postbaseline value prior to the study's last time point is used.†p=0.0003 vs. placebo

BONIVA 2.5 mg daily did not reduce the incidence of nonvertebral fractures (secondary efficacy measure). There was a similar number of nonvertebral osteoporotic fractures at 3 years reported in women treated with BONIVA 2.5 mg daily [9.1%, (95% CI: 7.1%, 11.1%)] and placebo [8.2%, (95% CI: 6.3%, 10.2%)]. The two treatment groups were also similar with regard to the number of fractures reported at the individual nonvertebral sites: pelvis, femur, wrist, forearm, rib, and hip.

Bone Mineral Density (BMD)

BONIVA significantly increased BMD at the lumbar spine and hip relative to treatment with placebo. In the 3-year osteoporosis treatment study, BONIVA 2.5 mg daily produced increases in lumbar spine BMD that were progressive over 3 years of treatment and were statistically significant relative to placebo at 6 months and at all later time points. Lumbar spine BMD increased by 6.4% after 3 years of treatment with 2.5 mg daily BONIVA compared with 1.4% in the placebo group. Table 4 displays the significant increases in BMD seen at the lumbar spine, total hip, femoral neck, and trochanter compared to placebo. Thus, overall BONIVA reverses the loss of BMD, a central factor in the progression of osteoporosis.

Table 4 Mean Percent Change in BMD from Baseline to Endpoint in Patients Treated Daily with BONIVA 2.5 mg or Placebo in the 3-Year Osteoporosis Treatment Study*
 | Placebo | BONIVA 2.5 mg Daily
Lumbar Spine | 1.4 (n=693) | 6.4 (n=712)
Total Hip | -0.7 (n=638) | 3.1 (n=654)
Femoral Neck | -0.7 (n=683) | 2.6 (n=699)
Trochanter | 0.2 (n=683) | 5.3 (n=699)

*The endpoint value is the value at the study's last time point, 3 years, for all patients who had BMD measured at that time; otherwise, the last postbaseline value prior to the study's last time point is used.

Bone Histology

The effects of BONIVA 2.5 mg daily on bone histology were evaluated in iliac crest biopsies from 16 women after 22 months of treatment and 20 women after 34 months of treatment.

The histological analysis of bone biopsies showed bone of normal quality and no indication of osteomalacia or a mineralization defect.

Once-Monthly Dosing

The effectiveness and safety of BONIVA once-monthly were demonstrated in a randomized, double-blind, multinational, noninferiority trial in 1602 women aged 54 to 81 years, who were on average 18 years postmenopause, and had L2-L4 lumbar spine BMD T-score below -2.5 SD at baseline. The main outcome measure was the comparison of the percentage change from baseline in lumbar spine BMD after 1 year of treatment with once-monthly ibandronate (100 mg, 150 mg) to daily ibandronate (2.5 mg). All patients received 400 IU vitamin D and 500 mg calcium supplementation per day.

BONIVA 150 mg once-monthly (n=327) was shown to be noninferior to BONIVA 2.5 mg daily (n=318) in lumbar spine BMD in a 1-year, double-blind, multicenter study of women with postmenopausal osteoporosis. In the primary efficacy analysis (per-protocol population), the mean increases from baseline in lumbar spine BMD at 1 year were 3.86% (95% CI: 3.40%, 4.32%) in the 2.5 mg daily group and 4.85% (95% CI: 4.41%, 5.29%) in the 150 mg once-monthly group; the mean difference between 2.5 mg daily and 150 mg once-monthly was 0.99% (95% CI: 0.38%, 1.60%), which was statistically significant (p=0.002). The results of the intent-to-treat analysis were consistent with the primary efficacy analysis. The 150 mg once-monthly group also had consistently higher BMD increases at the other skeletal sites compared to the 2.5 mg daily group.

14.2 Prevention of Postmenopausal Osteoporosis

Daily Dosing

The safety and effectiveness of BONIVA 2.5 mg daily for the prevention of postmenopausal osteoporosis were demonstrated in a randomized, double-blind, placebo-controlled 2-year study (Prevention Study) of 653 postmenopausal women without osteoporosis at baseline. Women were aged 41 to 82 years, were on average 8.5 years postmenopause, and had lumbar spine BMD T-scores >-2.5. Women were stratified according to time since menopause (1 to 3 years, >3 years) and baseline lumbar spine BMD (T-score: >-1, -1 to -2.5). The study compared daily BONIVA at three dose levels (0.5 mg, 1.0 mg, 2.5 mg) with placebo. All women received 500 mg of supplemental calcium per day.

The primary efficacy measure was the change in BMD of lumbar spine after 2 years of treatment. BONIVA 2.5 mg daily resulted in a mean increase in lumbar spine BMD of 3.1% compared with placebo following 2 years of treatment. Increases in BMD were seen at 6 months and at all later time points. Irrespective of the time since menopause or the degree of pre-existing bone loss, treatment with BONIVA resulted in a higher BMD response at the lumbar spine compared with placebo across all four baseline strata [time since menopause (1 to 3 years, >3 years) and baseline lumbar spine BMD (T-score: >-1, -1 to -2.5)].

Compared with placebo, treatment with BONIVA 2.5 mg daily increased BMD of the total hip by 1.8%, the femoral neck by 2.0%, and the trochanter by 2.1%.

Once-Monthly Dosing

BONIVA 150 mg once-monthly prevented bone loss in a majority (88.2%) of women in a randomized, double-blind, placebo-controlled 1-year study (Monthly Prevention Study) of 160 postmenopausal women with low bone mass at baseline (T-score of -1 to -2.5). Women, aged 46 to 60 years, were on average 5.4 years postmenopause. All women received 400 IU of vitamin D and 500 mg calcium supplementation daily.

The primary efficacy measure was the relative change in BMD at the lumbar spine after 1 year of treatment. BONIVA 150 mg once-monthly resulted in a mean increase in lumbar spine BMD of 4.12% (95% confidence interval 2.96 – 5.28) compared with placebo following 1 year of treatment (p<0.0001), based on a 3.73% and -0.39% mean change in BMD from baseline in the 150 mg once-monthly BONIVA and placebo treatment groups, respectively. BMD at other skeletal sites was also increased relative to baseline values.

16 HOW SUPPLIED/STORAGE AND HANDLING

Enter section text here

16.1 How Supplied

BONIVA 150 mg tablets: supplied as white, oblong, film-coated tablets, engraved with "BNVA" on one side and "150" on the other side. Packaged in

3 blister packs of 1 tablet each | NDC 54868-5322-0
1 blister pack of 1 tablet each | NDC 54868-5322-1

16.2 Storage and Handling

Store at 25°C (77°F); excursions permitted between 15° and 30°C (59° and 86°F) [see USP Controlled Room Temperature].

17 PATIENT COUNSELING INFORMATION

See FDA-APPROVED PATIENT LABELING (17.2)

17.1 Information for Patients

Patients should be instructed to read the Patient Information Leaflet carefully before taking BONIVA, to re-read it each time the prescription is renewed and to pay particular attention to the dosing instructions in order to maximize absorption and clinical benefit.

- BONIVA should be taken at least 60 minutes before the first food or drink (other than water) of the day and before taking any oral medication or supplementation including calcium, antacids or vitamins (see DRUG INTERACTIONS [7.1]).
- To facilitate delivery to the stomach, and thus reduce the potential for esophageal irritation, BONIVA tablets should be swallowed whole with a full glass of plain water (6 to 8 oz) while the patient is standing or sitting in an upright position. Patients should not lie down for 60 minutes after taking BONIVA.
- Patients should not eat, drink anything except for water, or take other medications for 60 minutes after taking BONIVA.
- Plain water is the only drink that should be taken with BONIVA. Note that some mineral waters may have a higher concentration of calcium and therefore should not be used.
- Patients should not chew or suck the tablet because of a potential for oropharyngeal ulceration.
- The BONIVA 2.5 mg tablet should be taken at the same time each day.
- If a once-daily dose is missed, the patient should be instructed to skip that dose and return to their normal schedule the next day.
- The patient must not take two 2.5 mg tablets within the same day.
- The BONIVA 150 mg tablet should be taken on the same date each month (i.e., the patient's BONIVA day).
- The patient must not take two 150 mg tablets within the same week.
- If the once-monthly dose is missed, and the patient's next scheduled BONIVA day is more than 7 days away, the patient should be instructed to take one BONIVA 150 mg tablet in the morning following the date that it is remembered (see DOSAGE AND ADMINISTRATION [2.3]). The patient should then return to taking one BONIVA 150 mg tablet every month in the morning of their chosen day, according to their original schedule.
- If the once-monthly dose is missed, and the patient's next scheduled BONIVA day is only 1 to 7 days away, the patient must wait until the subsequent month's scheduled BONIVA day to take their tablet. The patient should then return to taking one BONIVA 150 mg tablet every month in the morning of their chosen day, according to their original schedule.

Patients should receive supplemental calcium and vitamin D if dietary intake is inadequate. Intake of supplemental calcium and vitamin D should be delayed for at least 60 minutes following oral administration of BONIVA in order to maximize absorption of BONIVA.

Physicians should be alert to signs or symptoms signaling a possible esophageal reaction during therapy, and patients should be instructed to discontinue BONIVA and seek medical attention if they develop symptoms of esophageal irritation such as new or worsening dysphagia, pain on swallowing, retrosternal pain, or heartburn.

17.2 FDA-Approved Patient Labeling

Read this patient information carefully before you start taking BONIVA. Read this patient information each time you get a refill for BONIVA. There may be new information. This information is not everything you need to know about BONIVA. It does not take the place of talking with your health care provider about your condition or your treatment. Talk about BONIVA with your health care provider before you start taking it, and at your regular check-ups.

What is the most important information I should know about BONIVA?

BONIVA may cause serious problems in the stomach and the esophagus (the tube that connects your mouth and stomach) such as trouble swallowing, heartburn, and ulcers (see "What are the possible side effects of BONIVA?").

You must take BONIVA exactly as prescribed for BONIVA to work for you and to lower the chance of serious side effects (see "How should I take BONIVA?").

What is BONIVA?

BONIVA is a prescription medicine used to treat or prevent osteoporosis in women after menopause (see the end of this leaflet for "What is osteoporosis?").

BONIVA may reverse bone loss by stopping more loss of bone and increasing bone mass in most women who take it, even though they won't be able to see or feel a difference. BONIVA may help lower the chances of breaking bones (fractures).

For BONIVA to treat or prevent osteoporosis, you have to take it as prescribed. BONIVA will not work if you stop taking it.

Who should not take BONIVA?

Do not take BONIVA if you:

- have certain problems with your esophagus, the tube that connects your mouth and stomach
- cannot sit or stand up for at least 60 minutes
- have low blood calcium (hypocalcemia)
- are allergic to ibandronate sodium or any of the other ingredients of BONIVA (see the end of this leaflet for a list of all the ingredients in BONIVA)
- have kidneys that work very poorly

Tell your health care provider before using BONIVA:

- if you are pregnant or planning to become pregnant. It is not known if BONIVA can harm your unborn baby.
- if you are breast-feeding. It is not known if BONIVA passes into your milk and if it can harm your baby.
- have swallowing problems or other problems with your esophagus (the tube that connects your mouth and stomach)
- if you have kidney problems
- if you are planning a dental procedure such as tooth extraction

Tell your health care provider (including your dentist) about all the medicines you take including prescription and non-prescription medicines, vitamins and supplements. Some medicines, especially certain vitamins, supplements, and antacids can stop BONIVA from getting to your bones. This can happen if you take other medicines too close to the time that you take BONIVA (see "How should I take BONIVA?").

How should I take BONIVA?

- Take BONIVA exactly as instructed by your health care provider.
- Take BONIVA first thing in the morning at least 60 minutes before you eat, drink anything other than plain water, or take any other oral medicine.
- Take BONIVA with 6 to 8 ounces (about 1 full cup) of plain water. Do not take it with any drink other than plain water. Do not take it with other drinks, such as mineral water, sparkling water, coffee, tea, dairy drinks (such as milk), or juice.
- Swallow BONIVA whole. Do not chew or suck the tablet or keep it in your mouth to melt or dissolve.
- After taking BONIVA you must wait at least 60 minutes before: –Lying down. You may sit, stand, or do normal activities like read the newspaper or take a walk.–Eating or drinking anything except for plain water.–Taking other oral medicines including vitamins, calcium, or antacids. Take your vitamins, calcium, and antacids at a different time of the day from the time when you take BONIVA.
- If you take too much BONIVA, drink a full glass of milk and call your local poison control center or emergency room right away. Do not make yourself vomit. Do not lie down.
- Keep taking BONIVA for as long as your health care provider tells you. BONIVA will not work if you stop taking it.
- Your health care provider may tell you to exercise and take calcium and vitamin supplements to help your osteoporosis.
- Your health care provider may do a test to measure the thickness (density) of your bones or do other tests to check your progress.

What is my BONIVA schedule?

Schedule for taking BONIVA 2.5 mg once-daily:

- Take one BONIVA 2.5 mg tablet once a day first thing in the morning at least 60 minutes before you eat, drink anything other than plain water, or take any other oral medicine (see "How should I take BONIVA?").

What to do if I miss a daily dose:

- If you forget to take your BONIVA 2.5 mg tablet in the morning, do not take it later in the day. Just return to your normal schedule and take 1 tablet the next morning. Do not take two tablets on the same day.
- If you are not sure what to do if you miss a dose, contact your health care provider who will be able to advise you.

Schedule for taking BONIVA 150 mg once-monthly:

- Take one BONIVA 150 mg tablet once a month.
- Choose one date of the month (your BONIVA day) that you will remember and that best fits your schedule to take your BONIVA 150 mg tablet.
- Take one BONIVA 150 mg tablet in the morning of your chosen day (see "How should I take BONIVA?").

What to do if I miss a monthly dose:

- If your next scheduled BONIVA day is more than 7 days away, take one BONIVA 150 mg tablet in the morning following the day that you remember (see "How should I take BONIVA?"). Then return to taking one BONIVA 150 mg tablet every month in the morning of your chosen day, according to your original schedule.
- Do not take two 150 mg tablets within the same week. If your next scheduled BONIVA day is only 1 to 7 days away, wait until your next scheduled BONIVA day to take your tablet. Then return to taking one BONIVA 150 mg tablet every month in the morning of your chosen day, according to your original schedule.
- If you are not sure what to do if you miss a dose, contact your health care provider who will be able to advise you.

What should I avoid while taking BONIVA?

- Do not take other medicines, or eat or drink anything but plain water before you take BONIVA and for at least 60 minutes after you take it.
- Do not lie down for at least 60 minutes after you take BONIVA.

What are the possible side effects of BONIVA?

Stop taking BONIVA and call your health care provider right away if you have:

- pain or trouble with swallowing
- chest pain
- very bad heartburn or heartburn that does not get better

BONIVA MAY CAUSE:

- pain or trouble swallowing (dysphagia)
- heartburn (esophagitis)
- ulcers in your stomach or esophagus (the tube that connects your mouth and stomach)

Common side effects with BONIVA are:

- diarrhea
- pain in extremities (arms or legs)
- dyspepsia (upset stomach)

Less common side effects with BONIVA are short-lasting, mild flu-like symptoms (which usually improve after the first dose). These are not all the possible side effects of BONIVA. For more information ask your health care provider or pharmacist.

Rarely, patients have reported allergic and skin reactions. Contact your health care provider if you develop any symptoms of an allergic reaction including skin rash (with or without blisters), hives, wheezing, or swelling of the face, lips, tongue or throat. Get medical help right away if you have trouble breathing, swallowing or feel light-headed.

Rarely, patients have reported severe bone, joint, and/or muscle pain starting within one day to several months after beginning to take, by mouth, bisphosphonate drugs to treat osteoporosis (thin bones). This group of drugs includes BONIVA. Most patients experienced relief after stopping the drug. Contact your health care provider if you develop these symptoms after starting BONIVA.

Rarely, patients taking bisphosphonates have reported serious jaw problems associated with delayed healing and infection, often following dental procedures such as tooth extraction. If you experience jaw problems, contact your health care provider and dentist.

What is osteoporosis?

Osteoporosis is a disease that causes bones to become thinner. Thin bones can break easily. Most people think of their bones as being solid like a rock. Actually, bone is living tissue, just like other parts of the body, such as your heart, brain, or skin. Bone just happens to be a harder type of tissue. Bone is always changing. Your body keeps your bones strong and healthy by replacing old bone with new bone.

Osteoporosis causes the body to remove more bone than it replaces. This means that bones get weaker. Weak bones are more likely to break. Osteoporosis is a bone disease that is quite common in women after menopause. At first, osteoporosis has no symptoms, but people with osteoporosis may develop loss of height and are more likely to break (fracture) their bones, especially the back (spine), wrist, and hip bones.

Osteoporosis can be prevented, and with proper therapy it can be treated.

Who is at risk for osteoporosis?

Talk to your health care provider about your chances for getting osteoporosis.

Many things put people at risk for osteoporosis. The following people have a higher chance of getting osteoporosis:

Women who:

- are going through or who are past menopause ("the change")
- are white (Caucasian) or Asian

People who:

- are thin
- have a family member with osteoporosis
- do not get enough calcium or vitamin D
- do not exercise
- smoke
- drink alcohol often
- take bone thinning medicines (like prednisone) for a long time

General information about BONIVA

Do not use BONIVA for a condition for which it was not prescribed. Do not give BONIVA to other people, even if they have the same symptoms you have. It may harm them.

Store BONIVA at 77°F (25°C) or at room temperature between 59°F and 86°F (15°C and 30°C).

Keep BONIVA and all medicines out of the reach of children.

This summarizes the most important information about BONIVA. If you would like more information, talk with your health care provider. You can ask your health care provider or pharmacist for information about BONIVA that is written for health professionals.

For more information about BONIVA, call 1-888-MY-BONIVA or visit www.myboniva.com.

What are the ingredients of BONIVA?

BONIVA (active ingredient): ibandronate sodium

BONIVA (inactive ingredients): lactose monohydrate, povidone, microcrystalline cellulose, crospovidone, purified stearic acid, colloidal silicon dioxide, and purified water. The tablet film coating contains hypromellose, titanium dioxide, talc, polyethylene glycol 6000 and purified water.

BONIVA is a registered trademark of Roche Therapeutics Inc.

Distributed by:
Genentech USA, Inc.
A Member of the Roche Group
1 DNA Way
South San Francisco, CA 94080-4990

BAT_2005450_PI_AR2010_K(1)

Revised: January 2010

© 2010 Genentech, Inc. All rights reserved.

(see the HOW SUPPLIED section for complete listing)

Relabeling of "Additional Barcode Label" by:
Physicians Total Care, Inc.
Tulsa, OK 74146

PACKAGE LABEL

PRINCIPAL DISPLAY PANEL - 3 Pack Carton

once-monthly
Boniva®
(ibandronate sodium) Tablets

One tablet contains 168.75 mg ibandronate monosodium monohydrate,
equivalent to 150 mg free acid.

USUAL DOSAGE: For dosage recommendations and other important
prescribing information, read accompanying insert.

PHARMACIST: Dispense with important patient information.

150 mg
3 Packs–One Tablet Per Pack

Rx only